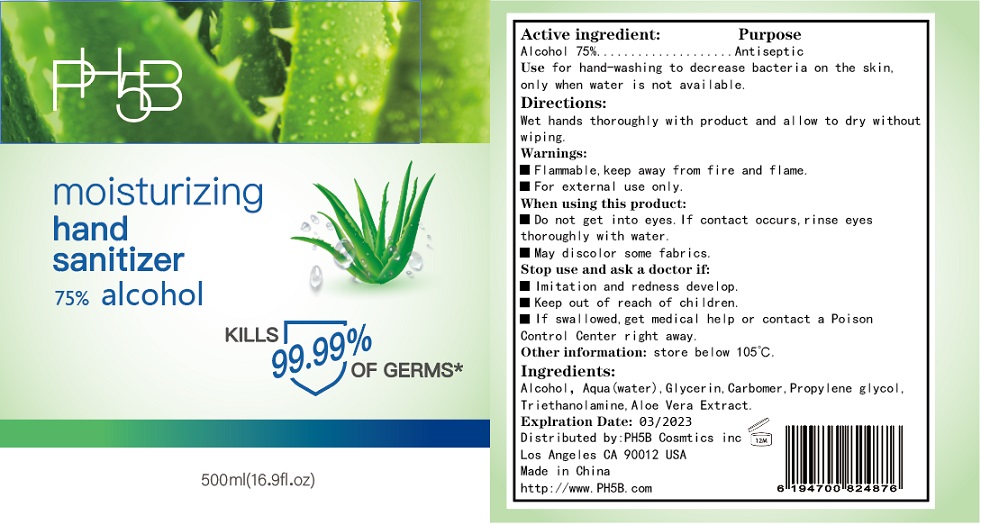 DRUG LABEL: PH5B Hand Sanitizer moisturizing
NDC: 76718-002 | Form: GEL
Manufacturer: Guangzhou Jukang Sanitary Products Co., Ltd.
Category: otc | Type: HUMAN OTC DRUG LABEL
Date: 20200609

ACTIVE INGREDIENTS: ALCOHOL 75 mL/100 mL
INACTIVE INGREDIENTS: WATER; CARBOMER INTERPOLYMER TYPE A (ALLYL SUCROSE CROSSLINKED); GLYCERIN; PROPYLENE GLYCOL; SODIUM HYDROXIDE

Active ingredient

Alcohol 75%

Purpose

Antiseptic

Use

For hand-washing to decrease bacteria on the skin, only when water is not available.

KEEP OUT OF REACH OF CHILDREN

if swallowed, get medical help or contact a Poison Control Center right away.

warnings:

Flamable, keep away from fire and flame

For external use only

When using this product, Do not get into eyes, if contact occurs, rinse eyes thoroughly with water.

Stop use and ask a doctor if irritation and redness develop.

Other information:

store below 105℉

Directions

- Wet hands thoroughly with product and allow to dry without wiping.

Inactive ingredients

Alcohol, aqua (water), glycerin, carbomer, triethanolamine, aloe vera extract